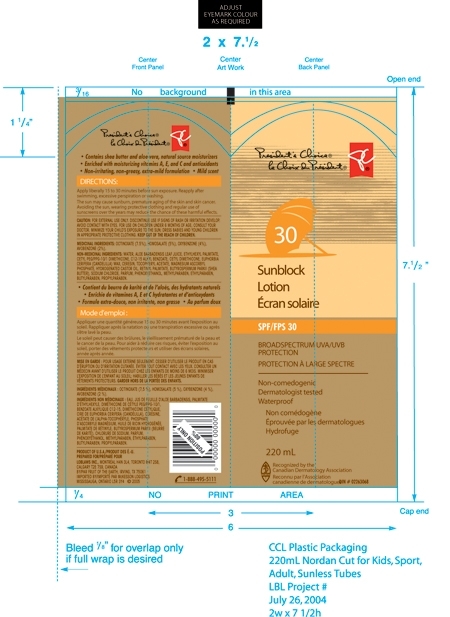 DRUG LABEL: Presidents Choice
NDC: 62217-152 | Form: LOTION
Manufacturer: Fruit of the Earth, Inc.
Category: otc | Type: HUMAN OTC DRUG LABEL
Date: 20100406

ACTIVE INGREDIENTS: Octinoxate 7.5 g/100 g; Homosalate 5 g/100 g; Oxybenzone 4 g/100 g; Avobenzone 2 g/100 g

Principal Display Panel

Enter section text here

President's Choice SPF/FPS 30 Sunblock Lotion

Broadspectrum UVA/UVB Protection

Non-comedogenic

Dermatologist tested

Waterproof

220 mL
Recognized by the Canadian Dermatology Association
DIN # 02263068

Directions

Enter section text here

Apply liberally 15 to 30 minutes before sun exposure. Reapply after swimming, excessive perspiration or washing.
The sun may cause sunburn, premature aging of the skin and skin cancer. Avoiding the sun, wearing protective clothing and regular use of sunscreens over the years may reduce the chance of these harmful effects.

CAUTION

Enter section text here

CAUTION: FOR EXTERNAL USE ONLY. DISCONTINUE USE IF SIGNS OF RASH OR IRRITATION DEVELOP. AVOID CONTACT WITH EYES. FOR USE ON CHILDREN UNDER 6 MONTHS OF AGE, CONSULT YOUR DOCTOR. MINIMIZE YOUR CHILD'S EXPOSURE TO THE SUN; DRESS BABIES AND YOUNG CHILDREN IN APPROPRIATE PROTECTIVE CLOTHING. KEEP OUT OF THE REACH OF CHILDREN.

Medicinal Ingredients

Enter section text here

MEDICINAL INGREDIENTS: OCTINOXATE (7.5%), HOMOSALATE (5%), OXYBENZONE (4%), AVOBENZONE (2%)